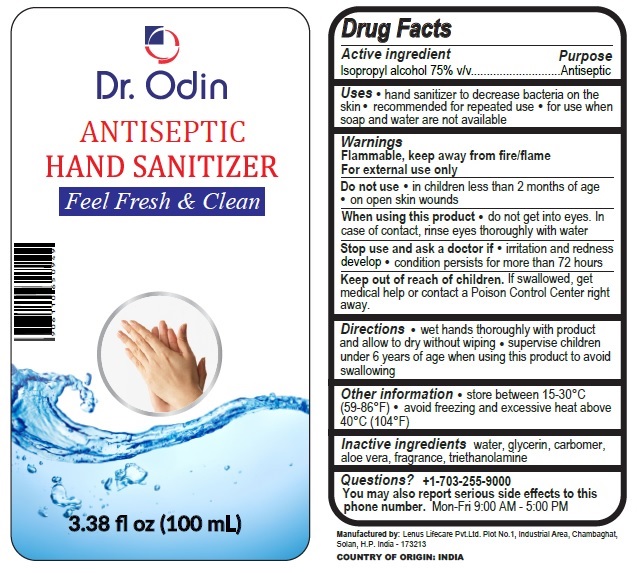 DRUG LABEL: Dr. Odin ANTISEPTIC HAND SANITIZER
NDC: 73820-110 | Form: LIQUID
Manufacturer: LENUS LIFE CARE PRIVATE LIMITED
Category: otc | Type: HUMAN OTC DRUG LABEL
Date: 20200411

ACTIVE INGREDIENTS: ISOPROPYL ALCOHOL 75 mL/100 mL
INACTIVE INGREDIENTS: WATER; GLYCERIN; CARBOMER HOMOPOLYMER, UNSPECIFIED TYPE; ALOE VERA LEAF; TROLAMINE

Dr. Odin ANTISEPTIC HAND SANITIZER

Active ingredient

Isopropyl alcohol 75% v/v

Purpose

Antiseptic

Uses

• hand sanitizer to decrease bacteria on the skin • recommended for repeated use • for use when soap and water are not available

Warnings

Flammable, keep away from fire/flame

For external use only

Do not use • in children less than 2 months of age • on open skin wounds

When using this product • do not get into eyes. In case of contact, rinse eyes thoroughly with water

Stop use and ask a doctor if • irritation and redness develop • condition persists for more than 72 hours

Keep out of reach of children. If swallowed, get medical help or contact a Poison Control Center right away.

Directions

• wet hands thoroughly with product and allow to dry without wiping • supervise children under 6 years of age when using this product to avoid swallowing

Other information

• store between 15-30°C (59-86°F) • avoid freezing and excessive heat above 40°C (104°F)

Inactive ingredients

water, glycerin, carbomer, aloe vera, fragrance, triethanolamine

Questions? +1-703-255-9000

You may also report serious side effects to this phone number. Mon-Fri 9:00 AM - 5:00 PM

Feel Fresh & Clean

Manufactured by: Lenus Lifecare Pvt.Ltd. Plot No.1, Industrial Area, Chambaghat, Solan, H.P. India - 173213

COUNTRY OF ORIGIN: INDIA